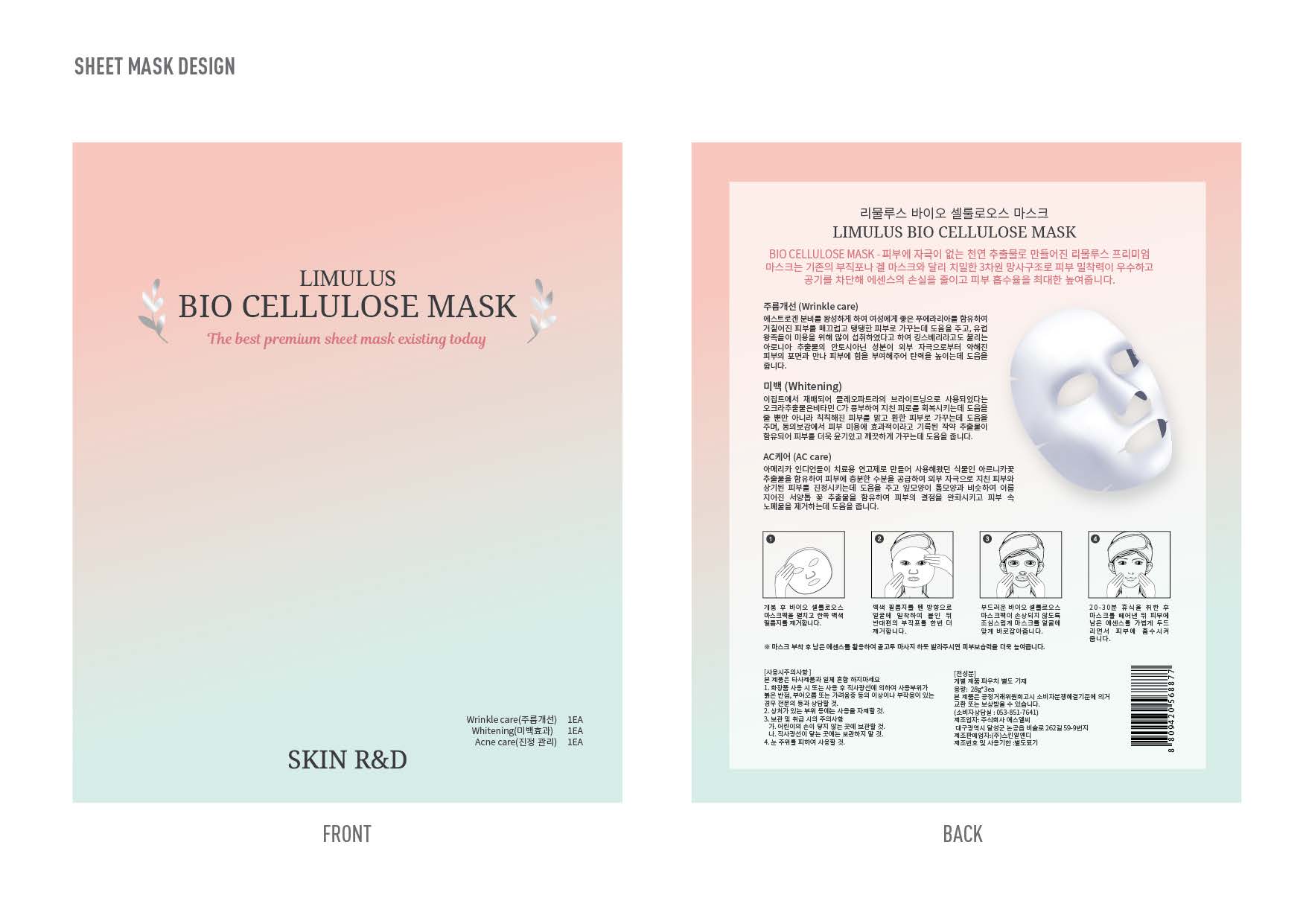 DRUG LABEL: Limulus Bio Cellulose Mask
NDC: 71464-0004 | Form: KIT | Route: TOPICAL
Manufacturer: Skin R&D
Category: otc | Type: HUMAN OTC DRUG LABEL
Date: 20170628

ACTIVE INGREDIENTS: ADENOSINE 0.04 g/100 g; NIACINAMIDE 2 g/100 g; GLYCERIN 16 g/100 g
INACTIVE INGREDIENTS: GLYCERIN; WATER; BUTYLENE GLYCOL; WATER; BUTYLENE GLYCOL; GLYCERIN; WATER; BUTYLENE GLYCOL

ACTIVE INGREDIENT

Glycerin, Niacinamide, Adenosine

INACTIVE INGREDIENT

Water, Butylene Glycol, etc

PURPOSE

Wrinkle Care, Whitening, AC Care

Keep out of reach of the children

INDICATIONS AND USAGE

1. Open the package and unfold the cellulose mask pack. Then, remove the white film.
2. Attach the product tightly on your face using the side where the white film was removed. Then, remove the fabric on the other side.
3. Carefully adjust the position of the mask on your face. Try not to damage the soft cellulose mask pack.
4. After taking 20-30 minutes of rest, remove the mask. Let your skin absorb the remaining essence with gently dabbing motion.

WARNINGS

1. Do not use in the following cases(Eczema and scalp wounds)
2.Side Effects
1)Due to the use of this druf if rash, irritation, itching and symptopms of hypersnesitivity occur dicontinue use and consult your phamacisr or doctor
3.General Precautions
1)If in contact with the eyes, wash out thoroughty with water If the symptoms are servere, seek medical advice immediately
2)This product is for exeternal use only. Do not use for internal use
4.Storage and handling precautions
1)If possible, avoid direct sunlight and store in cool and area of low humidity
2)In order to maintain the quality of the product and avoid misuse
3)Avoid placing the product near fire and store out in reach of children

DOSAGE AND ADMINISTRATION

for external use only